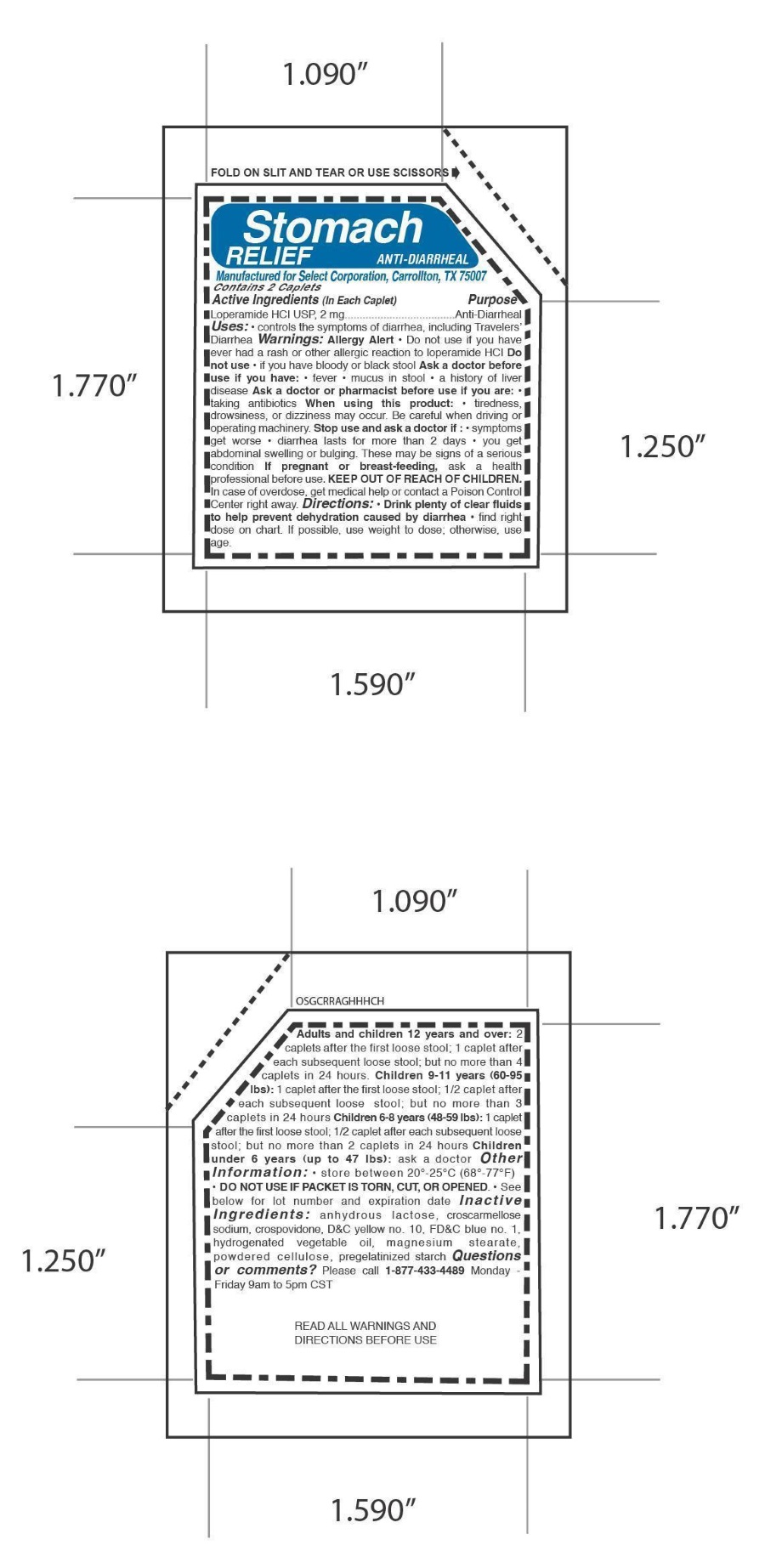 DRUG LABEL: Stomach Relief Anti Diarrheal
                
NDC: 52904-443 | Form: TABLET
Manufacturer: Select Corporation
Category: otc | Type: HUMAN OTC DRUG LABEL
Date: 20121015

ACTIVE INGREDIENTS: LOPERAMIDE HYDROCHLORIDE 2 mg/1 1
INACTIVE INGREDIENTS: LACTOSE; CROSCARMELLOSE SODIUM; CROSPOVIDONE; D&C YELLOW NO. 10; FD&C BLUE NO. 1; MAGNESIUM STEARATE; POWDERED CELLULOSE; STARCH, CORN

Drug Facts

ACTIVE INGREDIENT

Loperamide HCl 2 mg

PURPOSE

Anti Diarrheal

DOSAGE

Directions: • Drink plenty of clear fluids
to help prevent dehydration caused by diarrhea • find right
dose on chart. If possible, use weight to dose; otherwise, use
age.Adults and children 12 years and over: 2
caplets after the first loose stool; 1 caplet after
each subsequent loose stool; but no more than 4
caplets in 24 hours. Children 9-11 years (60-95
lbs): 1 caplet after the first loose stool; 1/2 caplet after
each subsequent loose stool; but no more than 3
caplets in 24 hours Children 6-8 years (48-59 lbs): 1 caplet
after the first loose stool; 1/2 caplet after each subsequent loose
stool; but no more than 2 caplets in 24 hours Children
under 6 years (up to 47 lbs): ask a doctor

INDICATIONS & USAGE

• controls the symptoms of diarrhea, including Travelers’ Diarrhea

WARNINGS

Allergy Alert

Do not use

• if you have ever had a rash or other allergic reaction to loperamide HCI

• if you have bloody or black stool Ask a doctor before use

• if you have: • fever • mucus in stool • a history of liver disease Ask a doctor or pharmacist before use

• if you are: • taking antibiotics When using this product: • tiredness, drowsiness, or dizziness may occur.

Be careful when driving or operating machinery.

Stop use and ask a doctor if :

• symptoms get worse

• diarrhea lasts for more than 2 days

• you get abdominal swelling or bulging.

These may be signs of a serious condition

PREGNANCY

If pregnant or breast-feeding, ask a health
professional before use.

KEEP OUT OF REACH OF CHILDREN.

INACTIVE INGREDIENT

Inactive
Ingredients: anhydrous lactose, croscarmellose sodium, crospovidone, DC yellow no. 10, FDC blue no. 1, hydrogenated vegetable oil, magnesium stearate, powdered cellulose, pregelatinized starch

LABEL DISPLAY PANEL

MM1